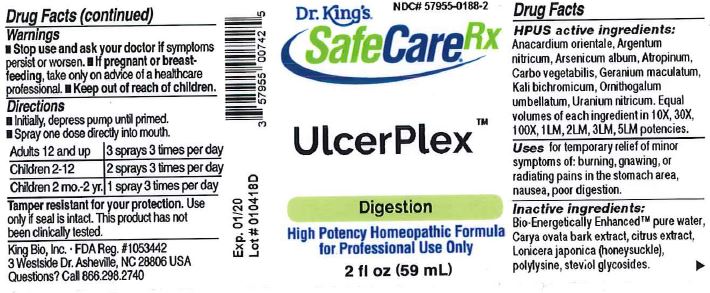 DRUG LABEL: UlcerPlex
NDC: 57955-0188 | Form: LIQUID
Manufacturer: King Bio Inc.
Category: homeopathic | Type: HUMAN OTC DRUG LABEL
Date: 20180216

ACTIVE INGREDIENTS: SEMECARPUS ANACARDIUM JUICE 10 [hp_X]/59 mL; SILVER NITRATE 10 [hp_X]/59 mL; ARSENIC TRIOXIDE 10 [hp_X]/59 mL; ATROPINE 10 [hp_X]/59 mL; ACTIVATED CHARCOAL 10 [hp_X]/59 mL; GERANIUM MACULATUM ROOT 10 [hp_X]/59 mL; POTASSIUM DICHROMATE 10 [hp_X]/59 mL; ORNITHOGALUM UMBELLATUM 10 [hp_X]/59 mL; URANYL NITRATE HEXAHYDRATE 10 [hp_X]/59 mL
INACTIVE INGREDIENTS: WATER; ANHYDROUS CITRIC ACID; POTASSIUM SORBATE

UlcerPlex™

ACTIVE INGREDIENT

Drug Facts__________________________________________________________________________________________________________

HPUS Active Ingredients: Anacardium orientale, Argentum nitricum, Arsenicum album, Atropinum, Carbo vegetabilis, Geranium maculatum, Kali bichromicum, Ornithogalum umbellatum, Uranium nitricum.

Equal volumes of each ingredient in 10X, 30X, 100X, 1LM, 2LM, 3LM, 5Lm potencies.

INDICATIONS AND USAGE

Uses for temporary relief of minor symptoms of: burning, gnawing, or radiating pains in the stomach area, nausea, poor digestion.

Inactive Ingredients:

Bio-Energetically Enhanced™ pure water, Carya ovata bark extract, citrus extract, Lonicera japonica (honeysuckle), polylysine, steviol glysocsides.

Warnings

- Stop use and ask your doctor if symptoms persist or worsen.
- If pregnant or breast-feeding, take only on advice of a healthcare professional.

- Keep out of reach of children.

Directions

- Initially, depress pump until primed.
- Spray one dose directly into mouth.
- Adults 12 and up: 3 sprays 3 times per day
- Children 2-12: 2 sprays 3 times per day
- Children 2mo.-2yr.: 1 spray 3 times per day

OTHER SAFETY INFORMATION

Tamper resistant for your protection. Use only if safety seal is intact. This product has not been clinically tested.

PURPOSE

Uses for temporary relief of minor symptoms of minor symptoms of:

- burning, gnawing, or radiating pains in the stomach area
- nausea
- poor digestion